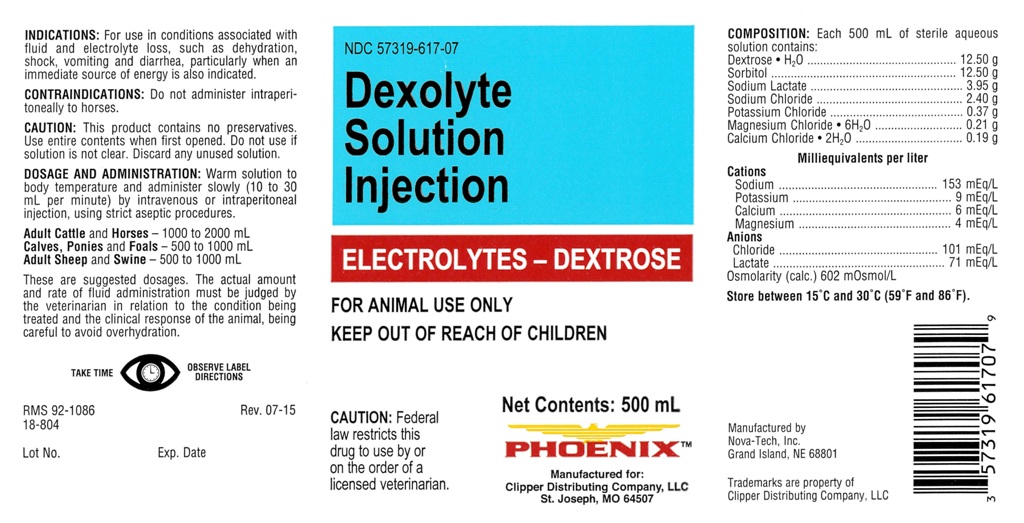 DRUG LABEL: Dexolyte Solution
NDC: 57319-617 | Form: INJECTION, SOLUTION
Manufacturer: Clipper
Category: animal | Type: PRESCRIPTION ANIMAL DRUG LABEL
Date: 20240605

ACTIVE INGREDIENTS: Dextrose Monohydrate 12.50 g/500 mL; Sorbitol 12.50 1/500 mL; Sodium Lactate 3.95 1/500 mL; Sodium Chloride 2.40 1/500 mL; Potassium Chloride 0.37 1/500 mL; Magnesium Chloride 0.21 1/500 mL; Calcium Chloride 0.19 1/500 mL

Dexolyte Solution Injection

INDICATIONS:

For use in conditions associated with
fluid and electrolyte loss, such as dehydration,
shock, vomiting and diarrhea, particularly when an
immediate source of energy is also indicated.

CONTRAINDICATIONS:

Do not administer intraperi-
toneally to horses.

CAUTION:

This product contains no preservatives.
Use entire contents when first opened. Do not use if
solution is not clear. Discard any unused solution.

DOSAGE AND ADMINISTRATION:

Warm solution to
body temperature and administer slowly (10 to 30
mL per minute) by intravenous or intraperitoneal
injection, using strict aseptic procedures.

Adult Cattle and Horses - 1000 to 2000 mL
Calves, Ponies and Foals - 500 to 1000 mLAdult Sheep and Swine - 500 to 1000 mL

These are suggested dosages. The actual amount
and rate of fluid administration must be judged by
the veterinarian in relation to the condition being
treated and the clinical response of the animal, being
careful to avoid overhydration.

PRECAUTIONS

TAKE TIME OBSERVE LABEL DIRECTIONS

INFORMATION FOR OWNERS/CAREGIVERS

RMS 92-1086 Rev. 07-15
18-804

Lot No. Exp. Date

Manufactured by
Nova-Tech, Inc.
Grand Island, NE 68801

Trademarks are property of
Clipper Distributing Company, LLC

Manufactured for:
Clipper Distributing Company, LLCSt. Joseph, MO 64507

Net Contents: 500 mL

ELECTROLYTES - DEXTROSE

VETERINARY INDICATIONS

FOR ANIMAL USE ONLY

KEEP OUT OF REACH OF CHILDREN

Caution:

Federal
law restricts this
drug to use by or
on the order of a
licensed veterinarian.

COMPOSITION:

Each 500 mL of sterile aqueous
solution contains:
Dextrose . H2O.........................12.50 g Sorbitol...................................12.50 g Sodium Lactate.........................3.95 g Sodium Chloride........................2.40 g Potassium Chloride....................0.37 g Magnesium Chloride . 6H2O.........0.21 g Calcium Chloride . 2H2O..............0.19 g

Milliequivalents per liter

Cations Sodium...................................153 mEq/LPotassium..................................9 mEq/LCalcium.....................................6 mEq/LMagnesium................................4 mEq/LAnions Chloride..................................101 mEq/LLactate.....................................71 mEq/LOsmolarity (calc.) 602 mOsmol/L

STORAGE AND HANDLING

Store between 15 degrees C and 30 degrees C (59 degrees F and 86 degrees F).